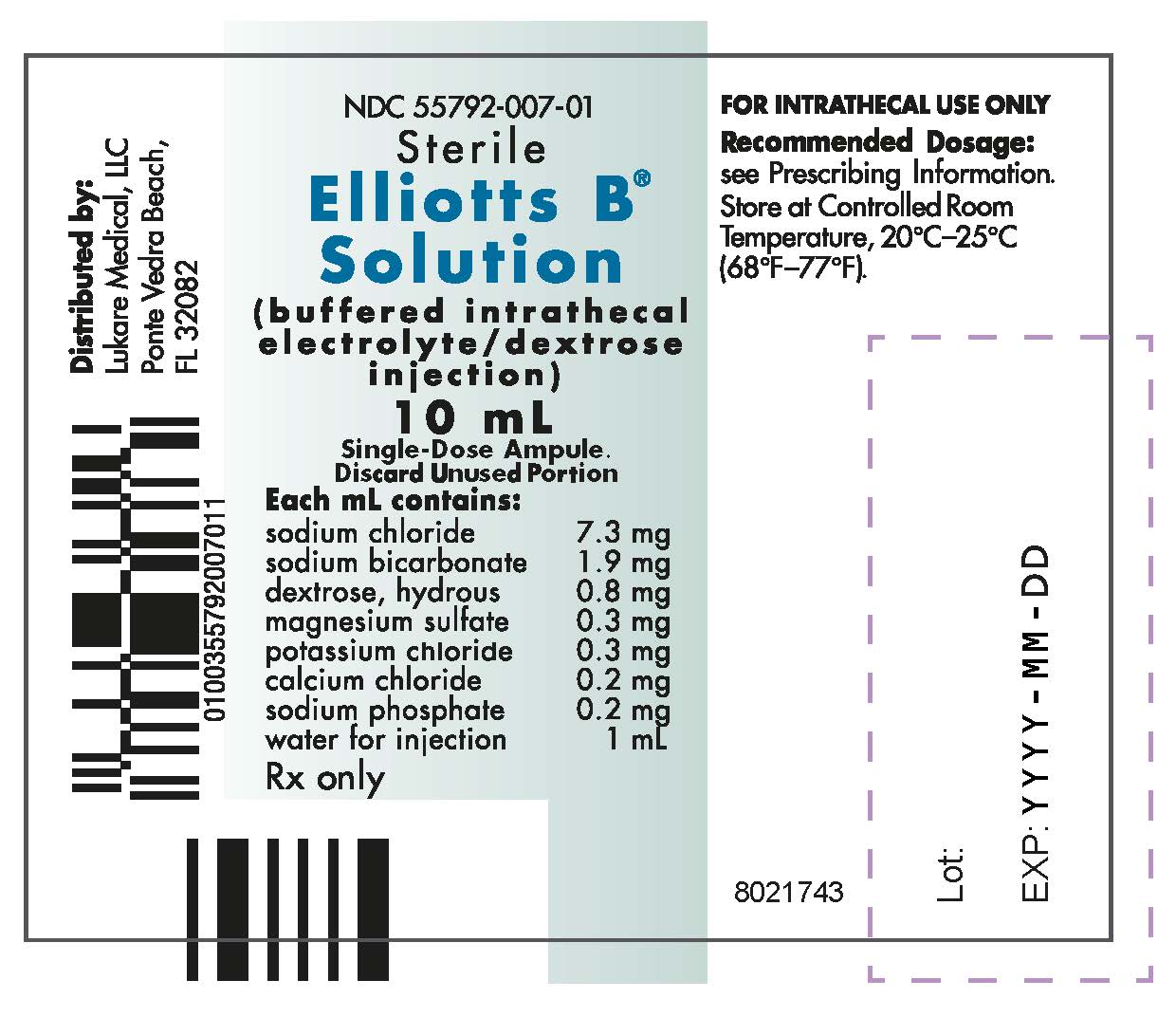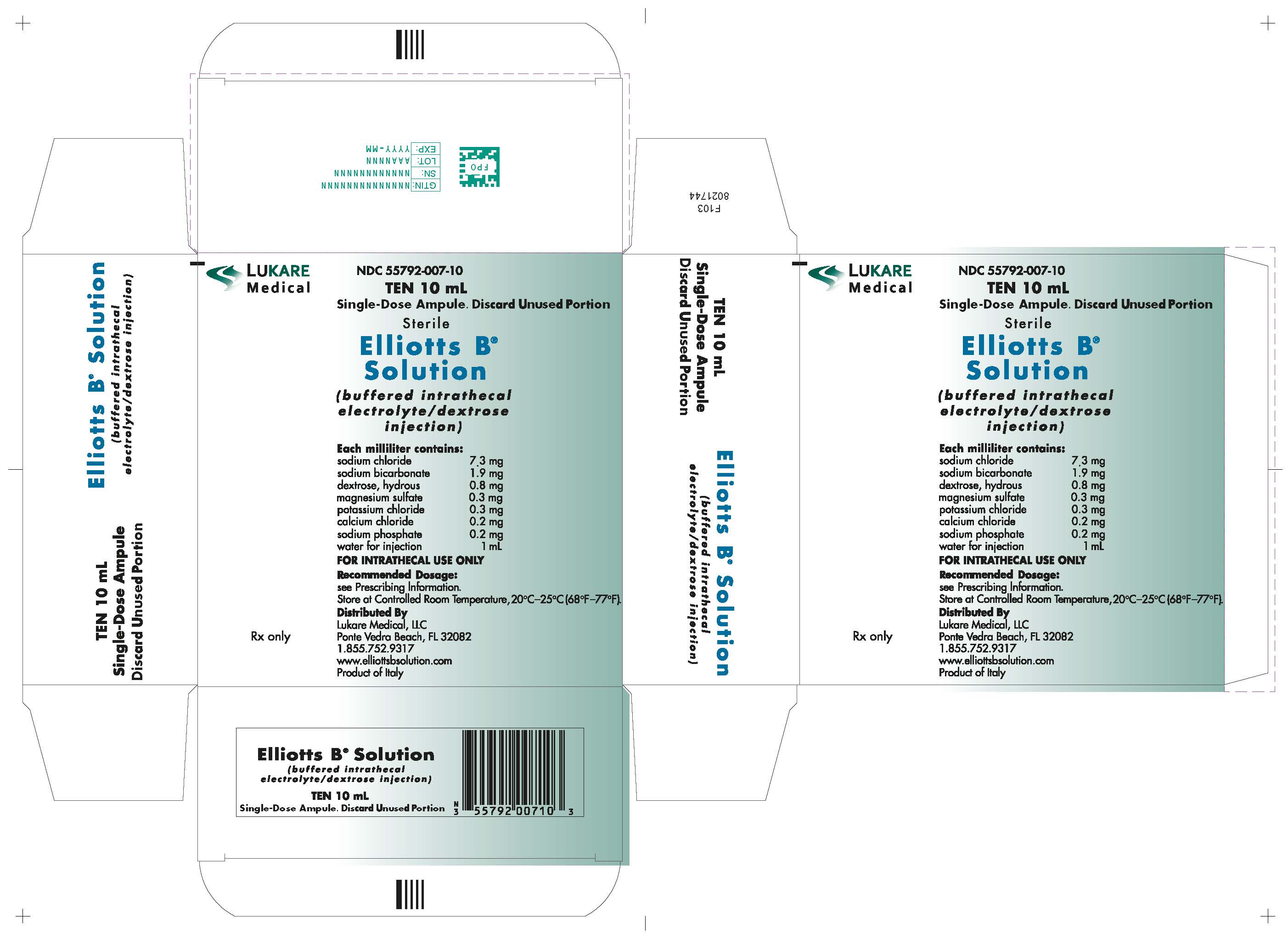 DRUG LABEL: Elliotts B
NDC: 55792-007 | Form: INJECTION
Manufacturer: Lukare Medical, LLC
Category: prescription | Type: HUMAN PRESCRIPTION DRUG LABEL
Date: 20241016

ACTIVE INGREDIENTS: sodium chloride 73 mg/10 mL; sodium bicarbonate 19 mg/10 mL; anhydrous dextrose 8 mg/10 mL; MAGNESIUM SULFATE, UNSPECIFIED FORM 3 mg/10 mL; potassium chloride 3 mg/10 mL; calcium chloride 2 mg/10 mL; sodium phosphate 2 mg/10 mL
INACTIVE INGREDIENTS: Water 10 mL/10 mL

ELLIOTTS B® SOLUTION (buffered intrathecal electrolyte/dextrose injection)
Rx Only

DESCRIPTION

Elliotts B® Solution is a sterile, nonpyrogenic, isotonic solution containing no bacteriostatic preservatives. Elliotts B Solution is a diluent for intrathecal administration of methotrexate sodium and cytarabine.

Each 10 mL of Elliotts B Solution contains:

Sodium Chloride, USP | 73 mg
Sodium Bicarbonate, USP | 19 mg
Dextrose, USP | 8 mg
Magnesium Sulfate • 7H2O, USP | 3 mg
Potassium Chloride, USP | 3 mg
Calcium Chloride • 2H2O, USP | 2 mg
Sodium Phosphate, dibasic • 7H2O, USP | 2 mg
Water for Injection, USP | qs 10 mL

Concentration of Electrolytes:

Sodium | 149 mEq/liter | Bicarbonate | 22.6 mEq/liter
Potassium | 4 mEq/liter | Chloride | 132 mEq/liter
Calcium | 2.7 mEq/liter | Sulfate | 2.4 mEq/liter
Magnesium | 2.4 mEq/liter | Phosphate | 1.5 mEq/liter

The formulae and molecular weights of the ingredients are:

INGREDIENT | MOLECULAR FORMULA | MOLECULAR WEIGHT
Sodium Chloride | NaCl | 58.44
Sodium Bicarbonate | NaHCO3 | 84.01
Dextrose | C6H12O6 | 180.16
Magnesium Sulfate • 7H2O | Mg2SO4 • 7H2O | 246.48
Potassium Chloride | KCl | 74.55
Calcium Chloride • 2H2O | CaCl2 • 2H2O | 147.01
Sodium Phosphate, dibasic • 7H2O | Na2HPO4 • 7H2O | 268.07

The pH of Elliotts B Solution is 6.0-7.5, and the osmolarity is 288 mOsmol per liter (calculated).

CLINICAL PHARMACOLOGY

Elliotts B Solution provides a buffered salt solution for use as a diluent for the intrathecal administration of methotrexate sodium and cytarabine. It has been demonstrated that Elliotts B Solution is comparable to cerebrospinal fluid in pH, electrolyte composition, glucose content, and osmolarity:

Comparison of Electrolyte Composition, pH and Nonelectrolytic Constituents of Elliotts B Solution and CSF

Solution | Na^+ mEq/L | K^+ mEq/L | Ca^++ mEq/L | Mg^++ mEq/L | HCO3^- mEq/L | Cl^- mEq/L | pH | Phosphorus mg/dL | Glucose mg/dL
Cerebrospinal Fluid | 117-137 | 2.3-4.6 | 2.2 | 2.2 | 22.9 | 113-127 | 7.31 | 1.2-2.1 | 45-80
Elliotts B Solution | 149 | 4 | 2.7 | 2.4 | 22.6 | 132 | 6.0-7.5 | 2.3 | 80

The approximate buffer capacity of Elliotts B Solution is 1.1 X 10^-2 equivalents when the challenge solution is 0.01 N HCl and 7.8 X 10^-3 equivalents when the challenge solution is 0.01 N NaOH.1

Compatibility studies with methotrexate sodium and cytarabine indicate these drugs are physically compatible with Elliotts B Solution.

INDICATIONS AND USAGE

Elliotts B Solution is indicated as a diluent for the intrathecal administration of methotrexate sodium and cytarabine for the prevention or treatment of meningeal leukemia or lymphocytic lymphoma.

CONTRAINDICATIONS

None known.

WARNINGS

Intrathecal administration of drugs such as methotrexate sodium and cytarabine should be performed by personnel skilled in the technique of lumbar puncture under the supervision of a physician who is experienced in the use of cancer chemotherapeutic agents. The labeling for methotrexate sodium and cytarabine should be consulted.

PRECAUTIONS

General

Particular attention should be taken to assure the maintenance of sterile technique throughout the procedure. (See DOSAGE AND ADMINISTRATION.)

Carcinogenesis, Mutagenesis, Impairment of Fertility

No standard mutagenicity or carcinogenicity studies have been conducted with Elliotts B Solution.

Usage in Pregnancy

All components of Elliotts B Solution are normal body constituents. Animal reproduction studies have not been conducted with Elliotts B Solution.

ADVERSE REACTIONS

Adverse reactions may occur with any given intrathecal injection due to the chemotherapy or the technique of intrathecal administration. (See product labeling for methotrexate sodium and cytarabine.)

Preservative-free methotrexate sodium and cytarabine should be used to minimize adverse reactions due to preservatives.

If an adverse reaction does occur, discontinue the administration, evaluate the patient, institute appropriate therapeutic countermeasures and, if possible, save the remainder of the unused solution(s) for examination.

DRUG ABUSE AND DEPENDENCE

There is no potential for drug abuse or drug dependence.

OVERDOSAGE

Elliotts B Solution is a diluent. In the event of a drug, fluid or solute overload following administration, evaluate the patient's condition, and institute appropriate corrective treatment. (See product labeling for methotrexate sodium and cytarabine.)

DOSAGE AND ADMINISTRATION

See product labeling for methotrexate sodium and cytarabine.

Elliotts B Solution is intended for intrathecal administration only. Elliotts B Solution does not contain antibacterial preservatives and introduction of contaminated solutions into the cerebrospinal fluid may have extremely serious consequences. Therefore, administration of intrathecal solutions should be accomplished as soon as possible after preparation.

A sterile filter-needle should be used to withdraw the contents of the ampule.

Intrathecal drug products should be inspected visually for particulate matter and discoloration prior to administration.

Preparation and Administration Precautions

Elliotts B Solution is a diluent for the cytotoxic anticancer agents, methotrexate sodium and cytarabine. Care should be exercised in the handling and preparation of infusion solutions with these products. (See product labeling for methotrexate sodium and cytarabine.)

HOW SUPPLIED

NDC | SIZE
55792-007-10 | 10 mL ampule

Elliotts B Solution is available in single-use clear glass ampules, packaged 10 ampules per box.
Store at controlled room temperature, 20ºC-25ºC (68ºF-77ºF) [See USP].
Preservative Free. Discard unused portion. Use only if solution is clear and ampule is intact.
Distributed by:
Lukare Medical, LLC
Ponte Vedra Beach, FL 32082
1-855-752-9317
www.elliottsbsolution.com

REFERENCES:

1. Cradock JC, et al. Evaluation of some pharmaceutical aspects of intrathecal methotrexate sodium, cytara‑bine and hydrocortisone sodium succinate. American Journal of Hospital Pharmacy (1978); 35:402.

Rev. 05/2024

PACKAGING

Ampule labeling:

Box labeling: